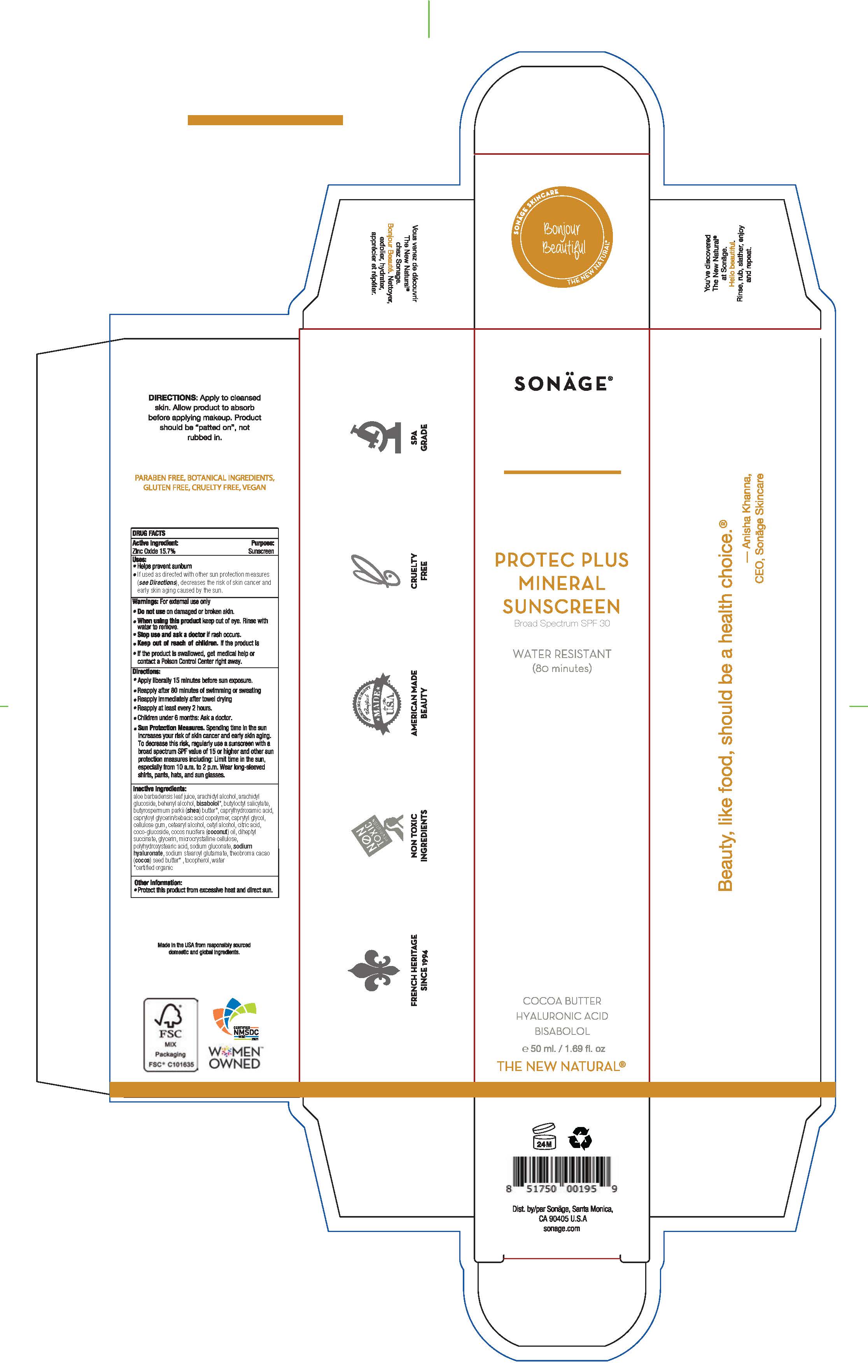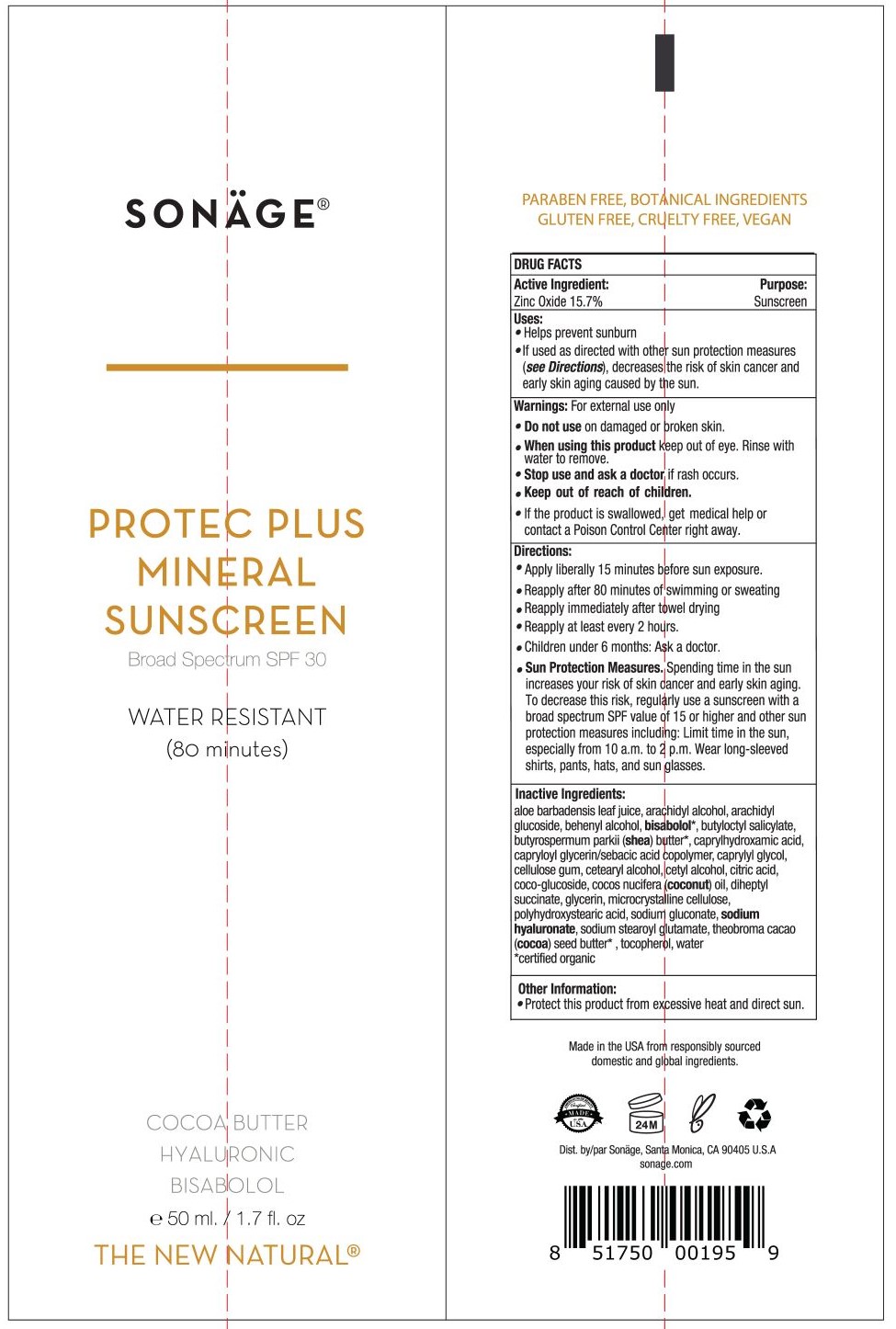 DRUG LABEL: Sonage Protec Plus SPF 30 Mineral Sunscreen
NDC: 69546-322 | Form: LOTION
Manufacturer: ASA Universal Inc. dba: Sonage
Category: otc | Type: HUMAN OTC DRUG LABEL
Date: 20241220

ACTIVE INGREDIENTS: ZINC OXIDE 15.7 g/100 mL
INACTIVE INGREDIENTS: LEVOMENOL; CETYL ALCOHOL; GLYCERIN; CAPRYLHYDROXAMIC ACID; CAPRYLOYL GLYCERIN/SEBACIC ACID COPOLYMER (2000 MPA.S); CARBOXYMETHYLCELLULOSE SODIUM, UNSPECIFIED; CITRIC ACID MONOHYDRATE; COCO GLUCOSIDE; COCONUT OIL; POLYHYDROXYSTEARIC ACID (2300 MW); SODIUM GLUCONATE; HYALURONATE SODIUM; CAPRYLYL GLYCOL; CETOSTEARYL ALCOHOL; DIHEPTYL SUCCINATE; ALOE VERA LEAF; ARACHIDYL ALCOHOL; ARACHIDYL GLUCOSIDE; DOCOSANOL; BUTYLOCTYL SALICYLATE; SHEA BUTTER; MICROCRYSTALLINE CELLULOSE; COCOA BUTTER; WATER; SODIUM STEAROYL GLUTAMATE; TOCOPHEROL

Sonage Protec Plus SPF 30 Mineral Sunscreen

ACTIVE INGREDIENT

Zinc Oxide - 15.7%

PURPOSE

Sunscreen

Uses

Helps prevent sunburn

If used as directed with other sun protection measures (see Directions), decreases the risk of skin cancer and early skin aging caused by the sun.

Warning

For external use only.

Do not use on damaged or broken skin.

When using this product keep out of eyes. Rinse with water to remove.

Stop use and ask a doctor if rash occurs.

Keep out of reach of children. If swallowed, get medical help or contact a Poison Control Center right away.

Directions

Apply liberally 15 minutes before sun exposure.

Reapply after 80 minutes of swimming or sweating

Reapply immediately after towel drying

Rapply at least every 2 hours.

Children under 6 monts: Ask a doctor.

Sun Protection Measures. Spending time in the sun increases your risk of skin cancer and early skin aging. To decrease this risk, regularly use a sunscreen with a broad spectrum SPF value of 15 or higher and other sun protection measures including: Limit time in the sun, especially from 10 a.m. to 2 p.m. Wear long-sleeved shirts, pants, hats, and sun glasses.

Inactive Ingredients

aloe barbadensis leaf juice, arachidyl alcohol, arachidyl glucoside, behenyl alcohol, bisabolol*, butyloctyl salicylate, butyrospermum parkii (shea) butter*, caprylhydroxamic acid, capryloyl glycerin/sebacic acid copolymer, caprylyl glycol, cellulose gum, cetearyl alcohol, cetyl alcohol, citric acid, coco-glucoside, cocos nucifera (coconut) oil, diheptyl succinate, glycerin, microcrystalline cellulose, polyhydroxystearic acid, sodium gluconate, sodiumhyaluronate, sodium stearoyl glutamate, theobroma cacao (cocoa) seed butter* , tocopherol, water
*certified organic

Other Information

Protect this product from excessive heat and direct sun.